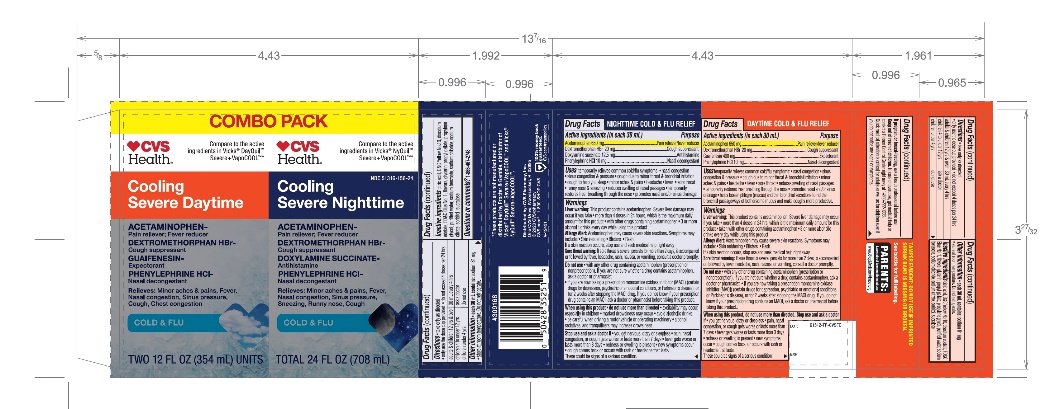 DRUG LABEL: CVS DayTime and NightTime Value Pack

NDC: 51316-156 | Form: KIT | Route: ORAL
Manufacturer: CVS PHARMACY
Category: otc | Type: HUMAN OTC DRUG LABEL
Date: 20251210

ACTIVE INGREDIENTS: ACETAMINOPHEN 650 mg/30 mL; DEXTROMETHORPHAN HYDROBROMIDE 20 mg/30 mL; GUAIFENESIN 400 mg/30 mL; PHENYLEPHRINE HYDROCHLORIDE 10 mg/30 mL; ACETAMINOPHEN 650 mg/30 mL; DEXTROMETHORPHAN HYDROBROMIDE 20 mg/30 mL; DOXYLAMINE SUCCINATE 12.5 mg/30 mL; PHENYLEPHRINE HYDROCHLORIDE 10 mg/30 mL
INACTIVE INGREDIENTS: ANHYDROUS CITRIC ACID; D&C YELLOW NO. 10; EDETATE DISODIUM; FD&C BLUE NO. 1; GLYCERIN; PROPYL GALLATE; PROPYLENE GLYCOL; WATER; SODIUM BENZOATE; SODIUM CHLORIDE; SODIUM CITRATE, UNSPECIFIED FORM; SORBITOL; SUCRALOSE; ANHYDROUS CITRIC ACID; D&C YELLOW NO. 10; EDETATE DISODIUM; FD&C BLUE NO. 1; GLYCERIN; PROPYL GALLATE; PROPYLENE GLYCOL; WATER; SODIUM BENZOATE; SODIUM CHLORIDE; SODIUM CITRATE, UNSPECIFIED FORM; SORBITOL; SUCRALOSE

CVS DayTime & NightTime Cold & Flu Combo pack

DayTime Cold & Flu

Active ingredients (in each 30 mL)

Acetaminophen 650 mg
Dextromethorphan HBr 20 mg
Guaifenesin 400 mg
Phenylephrine HCl 10 mg

Purpose

Pain reliever/Fever reducer
Cough suppressant
Expectorant
Nasal decongestant

Uses

- temporarily relieves common cold/flu symptoms:
- nasal congestion
- sinus congestion & pressure
- cough due to minor throat & bronchial irritation
- minor aches & pains
- headache
- fever
- sore throat
- reduces swelling of nasal passages
- temporarily restores freer breathing through the nose
- promotes nasal and/or sinus drainage
- helps loosen phlegm (mucus) and thin bronchial secretions to rid the bronchial passageways of bothersome mucus and make coughs more productive

Warnings

Liver warning

This product contains acetaminophen.

Severe liver damage may occur if you take

- more than 4 doses in 24 hours, which is the maximum daily amount for this product
- taken with other drugs containing acetaminophen
- 3 or more alcoholic drinks every day while using this product

Allergy Alert:

Acetaminophen may cause severe skin reactions. Symptoms may include:

- Skin reddening
- Blisters
- Rash

If a skin reaction occurs, stop use and seek medical help right away

Sore throat warning:

If sore throat is severe, persists for more than 2 days, is accompanied or followed by fever, headache, rash, nausea, or vomiting, consult a doctor promptly.

Do not use

- with any other drug containing acetaminophen (prescription or nonprescription). If you are not sure whether a drug contains acetaminophen, ask a doctor or pharmacist.
- if you are now taking a prescription monoamine oxidase inhibitor (MAOI) (certain drugs for depression, psychiatric or emotional conditions, or Parkinson's disease), or for 2 weeks after stopping the MAOI drug. If you do not know if your prescription drug contains an MAOI, ask a doctor or pharmacist before taking this product.

Ask a doctor or pharmacist before use if you aretaking the blood thinning drug warfarin.

When using this product, do not use more than directed.

Stop use and ask a doctor if

- you get nervous, dizzy or sleepless
- pain, nasal congestion, or cough gets worse or lasts more than 7 days
- fever gets worse or lasts more than 3 days
- redness or swelling is present
- new symptoms occur
- cough comes back or occurs with rash or headache that lasts.
  These could be signs of a serious condition.

PREGNANCY OR BREAST FEEDING

If pregnant or breast-feeding,ask a health professional before use.

Keep out of reach of children.In case of overdose, get medical help or contact a Poison Control Center right away. Quick medical attention is critical for adults as well as for children even if you do not notice any signs or symptoms.

Directions

- take only as directed
- Only use the dose cup provided
- do not exceed 4 doses per 24 hrs

adults & children 12 yrs & over | 30 mL every 4 hours
children 4 to under 12 yrs | ask a doctor
children under 4 yrs | do not use

Other information

each 30 mL contains:

- sodium 81 mg
- store at room temperature
- Do not refrigerate.

Inactive ingredients

Citric acid, D&C Yellow No. 10, disodium edetate, FD&C Blue No.1, flavor, glycerin, propyl gallate, propylene glycol, purified water, sodium benzoate, sodium chloride, sodium citrate, sorbitol, sucralose

Questions?

1-866-467-2748

NIGHTTIME COLD & FLU RELIEF

Active ingredients (in each caplet)

Acetaminophen 650 mg
Dextromethorphan HBr 20 mg
Doxylamine succinate 12.5 mg
Phenylephrine HCl 10 mg

Purpose

Pain reliever/Fever reducer
Cough suppressant
Antihistamine
Nasal decongestant

Uses

temporarily relieves common cold/flu symptoms:

- nasal congestion
- sinus congestion & pressure
- cough due to minor throat & bronchial irritation
- cough to help you sleep
- minor aches & pains
- headache
- fever
- sore throat
- runny nose & sneezing •reduces swelling of nasal passages
- temporarily restores freer breathing through the nose
- promotes nasal and/or sinus drainage

Warnings

Liver warning

This product contains acetaminophen.

Severe liver damage may occur if you take

- more than 4 doses in 24 hours, which is the maximum daily amount for this product
- taken with other drugs containing acetaminophen
- 3 or more alcoholic drinks every day while using this product

Allergy Alert:

acetaminophen may cause severe skin reactions.
Symptoms may include:

- Skin reddening
- Blisters
- Rash

If a skin reaction occurs, stop use and seek medical help right away

Sore throat warning:

If sore throat is severe, persists for more than 2 days, is accompanied or followed by fever, headache, rash, nausea, or vomiting, consult a doctor promptly.

Do not use

- with any other drug containing acetaminophen (prescription or nonprescription). If you are not sure whether a drug contains acetaminophen, ask a doctor or pharmacist.
- if you are now taking a prescription monoamine oxidase inhibitor (MAOI) (certain drugs for depression, psychiatric or emotional conditions, or Parkinson's disease), or for 2 weeks after stopping the MAOI drug. If you do not know if your prescription drug contains an MAOI, ask a doctor or pharmacist before taking this product.
- to make a child sleep

When using this product

- do not use more than directed
- excitability may occur, especially in children
- marked drowsiness may occur
- avoid alcoholic drinks
- be careful when driving a motor vehicle or operating machinery
- alcohol, sedatives & tranquilizers may increase drowsiness

Stop use and ask a doctor if

- you get nervous, dizzy or sleepless
- pain, nasal congestion, or cough gets worse or lasts more than 7 days
- fever gets worse or lasts more than 3 days
- redness or swelling is present
- new symptoms occur
- cough comes back or occurs with rash or headache that lasts.
  These could be signs of a serious condition.

PREGNANCY OR BREAST FEEDING

If pregnant or breast-feeding,ask a health professional before use.

Keep out of reach of children.In case of overdose, get medical help or contact a Poison Control Center right away. Quick medical attention is critical for adults as well as for children even if you do not notice any signs or symptoms.

Directions

- take only as directed
- Only use the dose cup provided
- do not exceed 4 doses per 24 hrs

adults & children 12 yrs & over | 30 mL every 4 hours
children 4 to under 12 yrs | ask a doctor
children under 4 yrs | do not use

Other information

- each 30 mL contains: sodium 81 mg
- Store at room temperature
- Do not refrigerate

Inactive ingredients

Citric acid, D&C Yellow No. 10, disodium edetate, FD&C Blue No.1, flavor, glycerin, propyl gallate, propylene glycol, purified water, sodium benzoate, sodium chloride, sodium citrate, sorbitol, sucralose

Questions?

1-866-467-2748

Distributed By:

PRINCIPAL DISPLAY PANEL - Kit Carton

**Compare to the active ingredients in Vicks®DayQuil™ Severe+ VapoCOOL™

NDC# 51316-156-24

DayTime

Cold & Flu

Relief

Acetaminophen – Pain reliever/Fever reducer

Dextromethorphan HBr – Cough suppressant

Guaifenesin - Expectorant

Phenylephrine HCl – Nasal decongestant

For Relief of

- Minor Aches & Pains, Fever
- Nasal Congestion & Sinus Pressure
- Cough
- Chest Congestion

*Compare to the active ingredients in Vicks®NyQuil™ Severe+ VapoCOOL™

NightTime

Cold & Flu

Relief

Acetaminophen – Pain reliever/Fever reducer

Dextromethorphan HBr – Cough suppressant

Phenylephrine HCl - Antihistamine

Phenylephrine HCl – Nasal decongestant

For Relief of

- Minor Aches & Pains, Fever
- Nasal Congestion & Sinus Pressure
- Sneezing, Runny Nose
- Cough

TWO BOTTLES, 12 FL OZ (354 mL) each; TOTAL 24 FL OZ (708 mL)

**This product is not manufactured or distributed by Procter & Gamble, distributor of Vicks®Dayquil™ Severe+ VapoCOOL™ and Vicks® Nyquil™ Severe+ VapoCOOL™